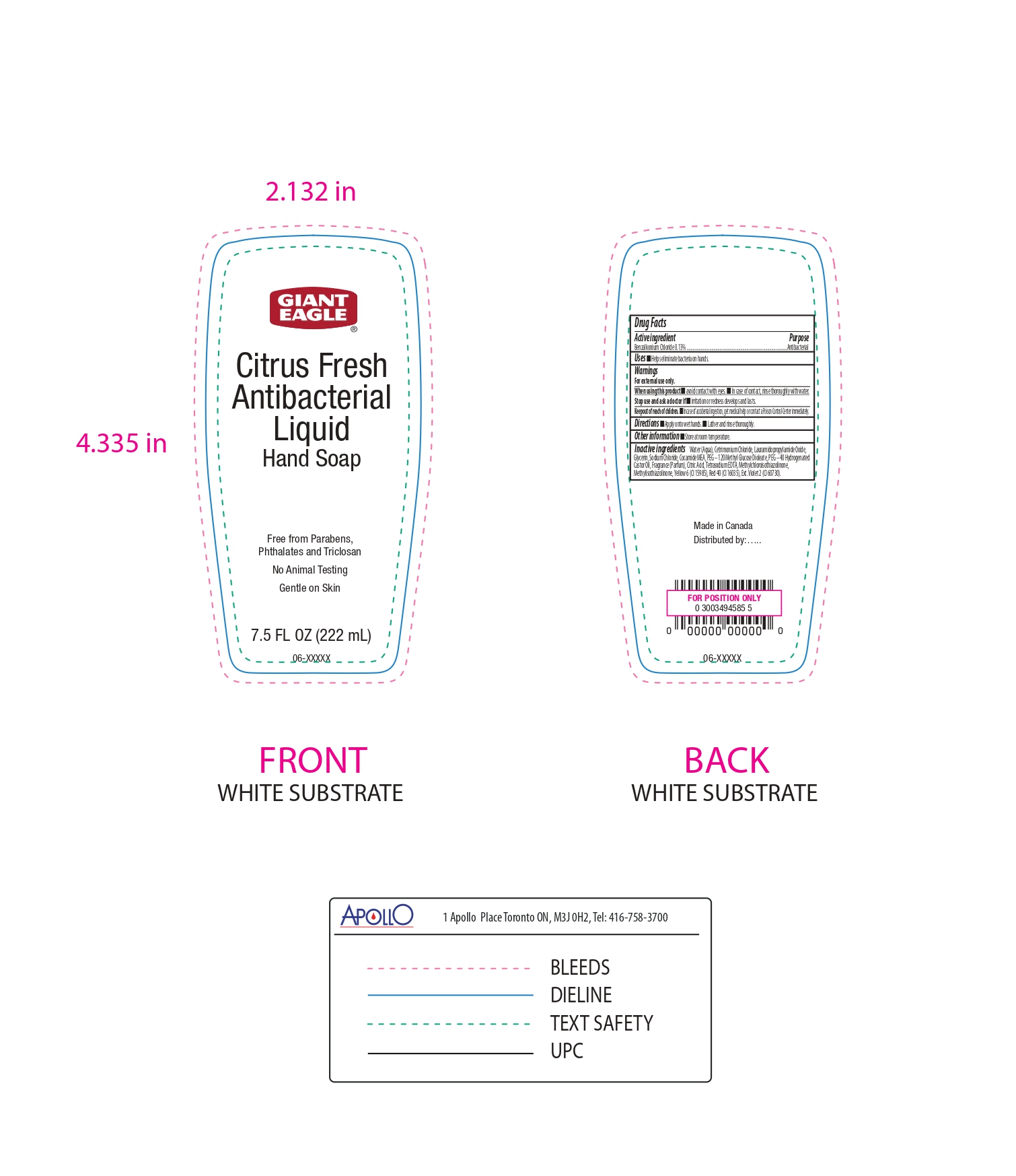 DRUG LABEL: Giant Eagle
NDC: 56194-501 | Form: SOAP
Manufacturer: GIANT EAGLE
Category: otc | Type: HUMAN OTC DRUG LABEL
Date: 20240612

ACTIVE INGREDIENTS: BENZALKONIUM CHLORIDE 130 mg/100 mL
INACTIVE INGREDIENTS: FD&C YELLOW NO. 6; GLYCERIN; PEG-40 CASTOR OIL; CETRIMONIUM CHLORIDE; SODIUM CHLORIDE; LAURAMIDOPROPYLAMINE OXIDE; EXT. D&C VIOLET NO. 2; METHYLCHLOROISOTHIAZOLINONE; WATER; METHYLISOTHIAZOLINONE; COCO MONOETHANOLAMIDE; PEG-120 METHYL GLUCOSE DIOLEATE; FRAGRANCE CLEAN ORC0600327; CITRIC ACID MONOHYDRATE; EDETATE SODIUM; FD&C RED NO. 40

Citrus Fresh Antibacterial Liq Hand Soap, 56194-501-01.

Active Ingredient.

Benzalkonium Chloride (0.13%)

Purpose

Antibacterial

Uses

Helps eliminate bacteria on hands.

Warnings

For external use only

When using this product

Avoid contact with eyes. In case of contact, rinse thoroughly with water.

Stop use and ask a doctor if

irritation or redness develops and lasts

Keep out of reach of children.

In case of accidental ingestion, get medical help or contact Poison Control Center immediately.

Directions

- Apply onto wet hands
- Lather and rinse thoroughly.

Other Information

Store at room temperature

Inactive Ingredients

Water (Aqua), Cetrimonium Chloride, Lauramidopropylamide Oxide, Glycerin, Sodium Chloride, Cocamide MEA, PEG – 120 Methyl Glucose Dioleate, PEG – 40 Hydrogenated Castor Oil, Fragrance (Parfum), Citric Acid, Tetrasodium EDTA, Methylchloroisothiazolinone, Methylisothiazolinone, Yellow 6 (CI 15985, Red 40 (CI 16035), Ext. Violet 2 (CI 60730).